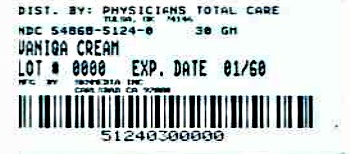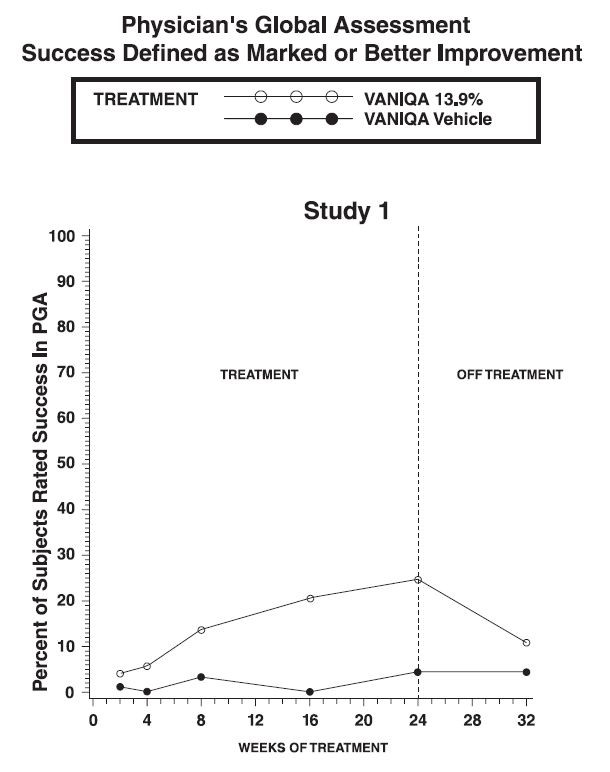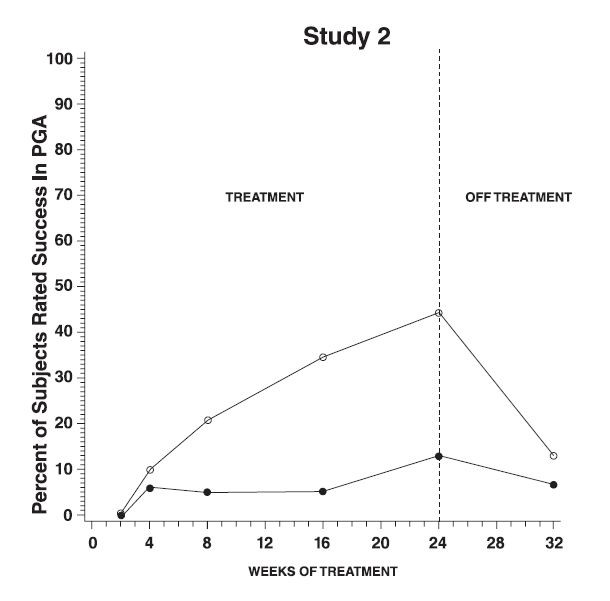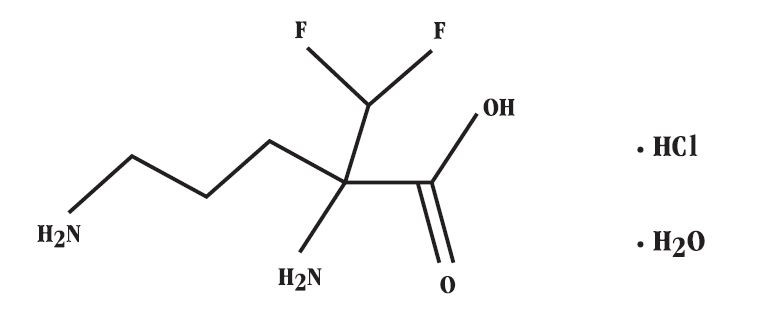 DRUG LABEL: VANIQA 
NDC: 54868-5124 | Form: CREAM
Manufacturer: Physicians Total Care, Inc.
Category: prescription | Type: HUMAN PRESCRIPTION DRUG LABEL
Date: 20120918

ACTIVE INGREDIENTS: Eflornithine Hydrochloride 139 mg/1 g
INACTIVE INGREDIENTS: Polyoxyl 20 Cetostearyl Ether; Cetostearyl Alcohol; Dimethicone; Glyceryl Monostearate; Methylparaben; Mineral Oil; Peg-100 Stearate; Phenoxyethanol; Propylparaben; Stearyl Alcohol; Water

Rx only
VANIQA® (eflornithine hydrochloride) Cream, 13.9%
For topical dermatological use only. Not for ophthalmic, oral or intravaginal use.

DESCRIPTION

VANIQA is a cream containing 13.9% (139 mg/g) of anhydrous eflornithine hydrochloride as eflornithine hydrochloride monohydrate (150 mg/g).

Chemically, eflornithine hydrochloride is (±) -2-(difluoromethyl) ornithine monohydrochloride monohydrate, with the empirical formula C 6H12F2N2O2• HCl•H2O, a molecular weight of 236.65 and the following structural formula:

Anhydrous eflornithine hydrochloride has an empirical formula C6H12F 2N2O2• HCl and a molecular weight of 218.65.

Other ingredients include: ceteareth-20, cetearyl alcohol, dimethicone, glyceryl stearate, methylparaben, mineral oil, PEG-100 stearate, phenoxyethanol, propylparaben, stearyl alcohol and water.

Pharmacodynamics

There are no studies examining the inhibition of the enzyme ornithine decarboxylase (ODC) in human skin following the application of topical eflornithine. However, there are studies in the literature that report the inhibition of ODC activity in skin following oral eflornithine. It is postulated that topical eflornithine hydrochloride irreversibly inhibits skin ODC activity. This enzyme is necessary in the synthesis of polyamines. Animal data indicate that inhibition of ornithine decarboxylase inhibits cell division and synthetic functions, which affect the rate of hair growth. VANIQA (eflornithine hydrochloride) Cream, 13.9% has been shown to retard the rate of hair growth in non-clinical and clinical studies.

Pharmacokinetics

The mean percutaneous absorption of eflornithine in women with unwanted facial hair, from a 13.9% w/w cream formulation, is < 1% of the radioactive dose, following either single or multiple doses under conditions of clinical use, that included shaving within 2 hours before radiolabeled dose application in addition to other forms of cutting or plucking and tweezing to remove facial hair. Steady state was reached within four days of twice-daily application. The apparent steady-state plasma t1/2 of eflornithine was approximately 8 hours. Following twice-daily application of 0.5 g of the cream (total dose 1.0 g/day; 139 mg as anhydrous eflornithine hydrochloride), under conditions of clinical use in women with unwanted facial hair (n=10), the steady-state Cmax, Ctrough and AUC12hr were approximately 10 ng/mL, 5 ng/mL, and 92 ng•hr/mL, respectively, expressed in terms of the anhydrous free base of eflornithine hydrochloride. At steady state, the dose-normalized peak concentrations (Cmax) and the extent of daily systemic exposure (AUC) of eflornithine following twice-daily application of 0.5 g of the cream (total dose 1.0 g/day) is estimated to be approximately 100and 60-fold lower, when compared to 370 mg/day once-daily oral doses. This compound is not known to be metabolized and is primarily excreted unchanged in the urine.

INDICATIONS AND USAGE

VANIQA (eflornithine hydrochloride) Cream, 13.9% is indicated for the reduction of unwanted facial hair in women.

VANIQA has only been studied on the face and adjacent involved areas under the chin of affected individuals. Usage should be limited to these areas of involvement.

CLINICAL TRIALS

Results of topical dermal studies for contact sensitization, photocontact sensitization, and photocontact irritation reveal that under conditions of clinical use, VANIQA is not expected to cause contact sensitization, phototoxic, or photosensitization reactions. Results of the topical dermal study for contact irritation did reveal that VANIQA could cause irritation reactions in clinical use in susceptible individuals or under conditions of exaggerated use.

Two randomized double-blind studies involving 594 female patients (393 treated with VANIQA, 201 with vehicle) treated twice daily for up to 24 weeks evaluated the efficacy of VANIQA in the reduction of unwanted facial hair in women. Women in the trial had a customary frequency of removal of facial hair two or more times per week. Women with facial conditions such as severe inflammatory acne, women who were pregnant, and nursing mothers were excluded from the studies. Physicians assessed the improvement or worsening from the baseline condition (Physician's Global Assessment [PGA]), 48 hours after shaving, of all treated areas. Statistically significant improvement for VANIQA (eflornithine hydrochloride) Cream, 13.9% versus vehicle was seen in each of these studies for "marked improvement" or greater response (24-week time point; p≤ 0.001). Marked improvement was seen consistently at 8 weeks after initiation of treatment and continued throughout the 24 weeks of treatment. Hair growth approached pretreatment levels within 8 weeks of treatment withdrawal. The success rate over time is graphically presented below for each pivotal trial.

Approximately 32% of patients showed marked improvement or greater (protocol definition of clinical success) after 24 weeks of treatment with VANIQA (eflornithine hydrochloride) Cream, 13.9%, compared to 8% with the vehicle. Combined results of these two trials through 24 weeks are presented below.

PGA Outcome | VANIQA | Vehicle
Clear/almost clear | 5% | 0%
Marked improvement | 27% | 8%
Improved | 26% | 26%
No improvement/worse/missing | 42% | 66%

Subgroup analyses appeared to suggest greater benefit for Whites than non-Whites (37% vs. 22% success, respectively; p=0.017). However, non-Whites, mostly Black subjects, did have significant treatment benefit with 22% graded as success on VANIQA compared to 5% on vehicle.

About 12% of women in the clinical trials were postmenopausal. Significant improvement in PGA outcome versus vehicle was seen in postmenopausal women (38% compared to 0%, p≤0.001).

VANIQA statistically significantly reduced how bothered patients felt by their facial hair and by the time spent removing, treating or concealing facial hair. These patient-observable differences were seen as early as 8 weeks after initiating treatment. Hair growth approached pretreatment levels within 8 weeks of treatment withdrawal.

Clinical trials with VANIQA involved over 1370 women with unwanted facial hair of skin types I-VI, of whom 68% were White, 17% Black, 11% Hispanic-Latino, 2% Asian-Pacific Islander, 0.6% American Native, and 1.3% other.

CONTRAINDICATIONS

VANIQA is contraindicated in patients with a history of sensitivity to any components of the preparation.

WARNINGS

Discontinue use if hypersensitivity occurs.

PRECAUTIONS

General

For external use only.
Transient stinging or burning may occur when applied to abraded or broken skin.

INFORMATION FOR PATIENTS

Patients using VANIQA should receive the following information and instructions:

1. This medication is not a depilatory, but rather appears to retard hair growth to improve the condition and the patient's appearance. Patients will likely need to continue using a hair removal method (e.g., shaving, plucking, etc.) in conjunction with VANIQA (eflornithine hydrochloride) Cream, 13.9%.
2. Onset of improvement was seen after as little as 4-8 weeks of treatment in the 24-week clinical trials. The condition may return to pretreatment levels 8 weeks after discontinuing treatment.
3. If skin irritation or intolerance develops, direct the patient to temporarily reduce the frequency of application (e.g., once a day). If irritation continues, the patient should discontinue use of the product.

Refer to the Patient Information Leaflet for additional important information and instructions.

DRUG INTERACTIONS

It is not known if VANIQA has any interaction with other topically applied drug products.

Carcinogenesis, Mutagenesis and Impairment of Fertility

In a 12-month photocarcinogenicity study in hairless albino mice, animals treated with the vehicle alone showed an increased incidence of skin tumors induced by exposure to ultraviolet (UVA/UVB) light, whereas mice treated topically with VANIQA at doses up to 600 mg/kg [19X the Maximum Recommended Human Dose (MRHD) based on body surface area (BSA)] showed an incidence of skin tumors equivalent to untreated-control animals.

A 2-year dermal carcinogenicity study in CD1 mice treated with VANIQA revealed no evidence of carcinogenicity at daily doses up to 600 mg/kg (950X the MRHD based on AUC comparisons).

Eflornithine did not elicit mutagenic effects in an Ames reverse-mutation assay or clastogenicity in primary human lymphocytes, with and without metabolic activation, In a dermal micronucleus assay, eflornithine hydrochloride cream, 13.9%, at doses up to 900 mg/kg (58X the MRHD based on BSA) in rats yielded no evidence of genotoxicity.

In a dermal fertility and early embryonic development study in rats treated with VANIQA, there were no adverse reproductive effects at doses up to 450 mg/kg (29X the MRHD based on BSA). In a peri- and postnatal study in rats, eflornithine administered in the drinking water was associated with maternal toxicity and reduced pup weights at doses of at least 625 mg/kg (40X the MRHD based on BSA) and a slightly reduced fertility index, which was considered to be of questionable biological significance, at 1698 mg/kg (110X the MRHD based on BSA). No effects were seen with an oral dose of 223 mg/kg (14X the MRHD based on BSA). In the latter study, the multiples of the human exposure are likely much higher, since eflornithine is well absorbed orally in rats, whereas minimal absorption occurs in humans treated topically.

Pregnancy

Teratogenic Effects: Pregnancy Category C
In the first dermal embryo-fetal development study in rats treated with eflornithine hydrochloride cream, 13.9% (in which no precautions were taken to prevent ingestion of drug from application sites), maternal toxicity and fetal effects including reduced numbers of live fetuses, decreased fetal weights, and delayed ossification and development of the viscera were observed at doses of 225 and 450 mg/kg (15X and 29X the MRHD based on BSA, respectively). When the study was repeated under conditions that avoided ingestion from application sites, no maternal, fetal or teratogenic effects were observed at doses up to 450 mg/kg (29X the MRHD based on BSA). In the first study in which no precautions were taken to prevent ingestion, circulating plasma levels were 11- to 14-fold higher than in the second study in which ingestion was prevented. In a dermal embryo-fetal development study in rabbits treated with VANIQA (eflornithine hydrochloride) Cream, 13.9% no adverse maternal or fetal effects occurred at doses up to 90 mg/kg (11X the MRHD based on BSA). Significant dermal irritation, as well as possible ingestion of VANIQA occurred at 300 mg/kg/day (36X the MRHD based on BSA) and was associated with maternal deaths, abortions, increased fetal resorptions, and reduced fetal weights, Fetotoxicity in the absence of maternal toxicity has been reported in oral studies with eflornithine with fetal no-effect doses of 80 mg/kg in rats and 45 mg/kg in rabbits. In these studies, no evidence of teratogenicity was observed in rats given up to 200 mg/kg or in rabbits given up to 135 mg/kg.

Although VANIQA was not formally studied in pregnant patients, 22 pregnancies occurred during the trials. Nineteen of these pregnancies occurred while patients were using VANIQA. Of the 19 pregnancies, there were 9 healthy infants, 4 spontaneous abortions, 5 induced/elective abortions, and 1 birth defect (Down's Syndrome to a 35-year-old). Because there are no adequate and well-controlled studies in pregnant women, the risk/benefit ratio of using VANIQA in women with unwanted facial hair who are pregnant should be weighed carefully with serious consideration for either not implementing or discontinuing use of VANIQA.

Nursing Mothers

It is not known whether or not eflornithine hydrochloride is excreted in human milk. Caution should be exercised when VANIQA is administered to a nursing woman.

Pediatric Use

The safety and effectiveness of this product have not been established in pediatric patients less than 12 years of age.

Geriatric Use

Of the 1373 patients on active treatment in clinical studies of VANIQA, approximately 7% were 65 years or older and approximately 1% were 75 or older. No apparent differences in safety were observed between older patients and younger patients.

ADVERSE REACTIONS

Adverse events reported for most body systems occurred at similar frequencies in VANIQA (eflornithine hydrochloride) Cream, 13.9% and vehicle control groups, The most frequent adverse events related to treatment with VANIQA were skin-related, The following table notes the percentage of adverse events associated with the use of VANIQA or its vehicle that occurred at greater than 1% in both the vehicle controlled studies and the open-label safety studies up to 1 year of continuous use.

Adverse Event Term | Vehicle-Controlled Studies |  | Vehicle-Controlled and Open-Label Studies
Adverse Event Term | VANIQA; (n=393) | Vehicle; (n=201) | VANIQA; (n=1373)
Acne | 21.3 | 21.4 | 10,8
Pseudofolliculitis Barbae | 16.3 | 15.4 | 4.9
Stinging Skin | 7.9 | 2.5 | 4.1
Headache | 3.8 | 5.0 | 4.0
Burning Skin | 4.3 | 2.0 | 3.5
Dry Skin | 1.8 | 3.0 | 3.3
Pruritus (itching) | 3.8 | 4.0 | 3.1
Erythema (redness) | 1.3 | 0.0 | 2.5
Tingling Skin | 3.6 | 1.5 | 2.2
Dyspepsia | 2.5 | 2.0 | 1.9
Skin Irritation | 1.0 | 1.0 | 1.8
Rash | 2.8 | 0.0 | 1.5
Alopecia | 1.5 | 2.5 | 1.3
Dizziness | 1.5 | 1.5 | 1.3
Folliculitis | 0.5 | 0.0 | 1.0
Hair Ingrown | 0.3 | 2.0 | 0.9
Facial Edema | 0.3 | 3.0 | 0.7
Anorexia | 1.0 | 2.0 | 0.7
Nausea | 0.5 | 1.0 | 0.7
Asthenia | 0.0 | 1.0 | 0.3
Vertigo | 0.3 | 1.0 | 0.1

Treatment-related skin adverse events that occurred in less than 1% of the subjects treated with VANIQA are: bleeding skin, cheililis, contact dermatitis, swelling of lips, herpes simplex, numbness and rosacea.

Adverse events were primarily mild in Intensity and generally resolved without medical treatment or discontinuation of VANIQA. Only 2% of subjects discontinued studies due to an adverse event related to use of VANIQA.

Laboratory Test Abnormalities

No laboratory test abnormalities have been consistently found to be associated with VANIQA. In an open-label study, some patients showed an increase in their transaminases; however, the clinical significance of these findings is not known.

OVERDOSAGE

Overdosage information with VANIQA is unavailable. Given the low percutaneous penetration of this drug, overdosage via the topical route is not expected (see CLINICAL PHARMACOLOGY). However, should very high topical doses (e.g., multiple tubes per day) or oral ingestion be encountered (a 30 g tube contains 4.2 g of eflornithine hydrochloride), the patient should be monitored, and appropriate supportive measures administered as necessary.

(Note: Use of an intravenous formulation of eflornithine hydrochloride at high doses (400 mg/kg/day or approximately 24 g/day) for the treatment of Trypanosoma brucei gambiense infection (African sleeping sickness) has been associated with adverse events and laboratory abnormalities. Adverse events in this setting have included hair loss, facial swelling, seizures, hearing impairment, stomach upset, loss of appetite, headache, weakness and dizziness. A variety of hematological toxicities, including anemia, thrombocytopenia and leukopenia have also been observed, but these were usually reversible upon discontinuation of treatment.)

DOSAGE & ADMINISTRATION

Apply a thin layer of VANIQA (eflornithine hydrochloride) Cream, 13.9% to affected areas of the face and adjacent involved areas under the chin and rub in thoroughly. Do not wash treated area for at least 4 hours. Use twice daily at least 8 hours apart or as directed by a physician. The patient should continue to use hair removal techniques as needed in conjunction with VANIQA. (VANIQA should be applied at least 5 minutes after hair removal.) Cosmetics or sunscreens may be applied over treated areas after cream has dried.

HOW SUPPLIED

VANIQA (eflornithine hydrochloride) Cream, 13.9% is available as:
30 gram tube
NDC 54868-5124-0

STORAGE

Store at 25°C (77°F); excursions permitted to 15°C-30°C (59°F-86°F) [See USP Controlled Room Temperature] Do not freeze. See tube crimp and carton end for expiration date and lot number.

Rx Only
Distributed By:
SkinMedica, Inc. Carlsbad, CA 92010
www.skinmedica.com 1-877-3VANIQA
U.S. Patent Number 5,648,394

Additional barcode labeling by:
Physicians Total Care, Inc.
Tulsa, Oklahoma 74146

Patient Information Leaflet for

VANIQA®
(eflornithine hydrochloride) Cream, 13.9%

INFORMATION FOR PATIENTS

This section contains important information about VANIQA that you should read before you begin treatment. This section does not list all the benefits and risks of VANIQA and does not take the place of discussions with your doctor or healthcare professional about your condition or your treatment. If you have questions, talk with your healthcare professional. The medicine described here can only be prescribed by a licensed healthcare professional. Only your healthcare professional can determine if VANIQA is right for you.

What is VANIQA?
VANIQA (pronounced "VAN-i-ka") is a prescription medication applied to the skin for the reduction of unwanted facial hair in women.

The active ingredient in VANIQA is eflornithine hydrochloride. VANIQA also contains ceteareth-20, cetearyl alcohol, dimethicone, glyceryl stearate, methylparaben, mineral oil, PEG-100 stearate, phenoxyethanol, propylparaben, stearyl alcohol and water.

How does VANIQA work?
VANIQA interferes with an enzyme found in the hair follicle of the skin needed for hair growth. This results in slower hair growth and improved appearance where VANIQA is applied.

VANIQA does not permanently remove hair or "cure" unwanted facial hair. It is not a depilatory. Your treatment program should include continuation of any hair removal technique you are currently using. VANIQA will help you manage your condition and improve your appearance.

Improvement in the condition occurs gradually. Don't be discouraged if you see no immediate improvement. Be patient. Improvement may be seen as early as 4 to 8 weeks of treatment. Improvement may take longer in some individuals. If no improvement is seen after 6 months of use, discontinue use. Clinical studies show that in about 8 weeks after stopping treatment with VANIQA, the hair will return to the same condition as before beginning treatment.

Who should not use VANIQA?
You should not use VANIQA if you are allergic to any of the ingredients in the cream. All ingredients are listed on the tube and at the beginning of this leaflet.

You should not use VANIQA if you are less than 12 years of age.

What should you tell your doctor before using VANIQA?
If you are allergic to any of the ingredients, tell your doctor.

If you are pregnant or plan to become pregnant, discuss with your doctor whether you should use VANIQA during pregnancy. No clinical studies have been performed in pregnant women.

If you are breastfeeding, consult your doctor before using VANIQA. It is not known if VANIQA is passed to infants through breast milk.

If you are taking any prescription medicines, non-prescription medicines or using any facial or skin creams, check with your physician before use of VANIQA.

How should I use VANIQA?
Use VANIQA only for the condition for which it was prescribed by your doctor. Do not give it to other people or allow other people to use it.

You will need to continue your normal procedures for hair removal until desired results have been achieved. You may then be less bothered by the time spent in removing hair or the frequency of hair removal. VANIQA is to be used twice daily, at least eight hours apart, or as directed by your doctor. VANIQA is for external use only.

Follow the instructions for application of VANIQA carefully. Apply a thin layer of VANIQA to the affected areas of the face and adjacent involved areas under the chin and rub in thoroughly. You should not wash the treatment areas for at least 4 hours after application of VANIQA.

VANIQA® may cause temporary redness, rash, burning, stinging or tingling, especially when the skin is damaged. If irritation continues, stop use of VANIQA and contact your doctor. Avoid getting the medication in your eyes or inside your nose or mouth. If the product gets in your eyes, rinse thoroughly with water and contact your doctor.

If you forget or miss a dose of VANIQA, do not try to “make it up”. Return to your normal application schedule as soon as you can.

You may use your normal cosmetics or sunscreen after applying VANIQA, but you should wait a few minutes to allow the treatment to be absorbed before applying them.

If your condition gets worse with treatment, stop use of VANIQA and contact your doctor.

What are the possible side effects of VANIQA?
VANIQA may cause temporary redness, stinging, burning, tingling or rash on areas of the skin where it is applied. Folliculitis (hair bumps) may also occur. If these persist, consult your doctor.

How should VANIQA be stored?
VANIQA should be stored at 15°C-30° C (59° F-86° F). Do not freeze.
Keep this and all medicines out of the reach of children.

This medicine was prescribed for your particular condition. Do not use it for another condition or give it to anyone else.

This summary does not include everything there is to know about VANIQA. If you have questions or concerns, or want more information about VANIQA, your doctor or pharmacist has the complete prescribing information upon which this leaflet is based. You may want to read it and discuss it with your doctor or healthcare professional. Remember, no written summary can replace careful discussion with your doctor.

Rx Only
Distributed By:
SkinMedica, Inc.
Carlsbad, CA 92010
www.skinmedic.com
1-877-3VANIQA
U.S. Patent Number 5,648,394

PACKAGE LABEL

NDC 54868-5124-0
VANIQA®(eflornithine hydrochloride)
Cream, 13.9%
Rx only
SkinMedica®
Net Wt 30g / 1.06 oz

Warning: Keep out of reach of children.

Each gram contains: 13.9% (139 mg/g) of anhydrous eflornithine hydrochloride as eflornithine hydrochloride monohydrate (150 mg/g) in a cream base of ceteareth-20, cetearyl alcohol, dimethicone, glyceryl stearate, methylparaben, mineral oil, PEG-100 stearate, phenoxyethanol, propylparaben, stearyl alcohol and water.

Store at 25° C (77° F); excursions permitted to 15° C-30° C (59° F-86°F) [see USP Controlled Room Temperature]. Do not freeze.

Distributed by
SkinMedica, Inc.
Carlsbad, California 92010, USA
Made in Canada
www.skinmedica.com
1-877-3VANIQA
Revised 3/2011 2005445

For topical dermatologic use only.
Not for ophthalmic,oral or intravaginal use.

See bottom flap of carton and crimp of tube for Lot Number and Expiration Date.

Usual Dosage: Apply to affected area twice daily. See package insert for complete information.

U.S. Patent No. 5,648,394